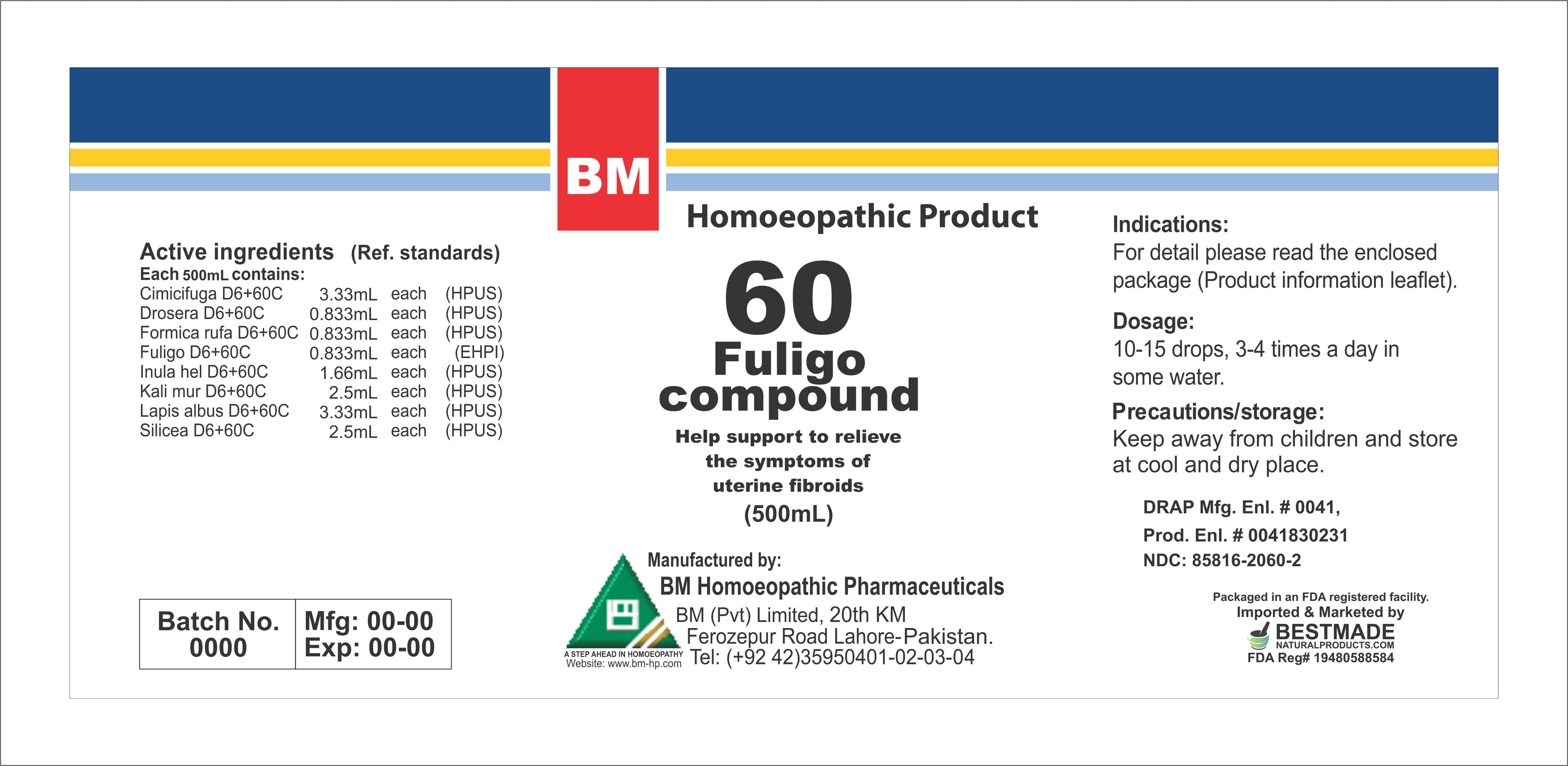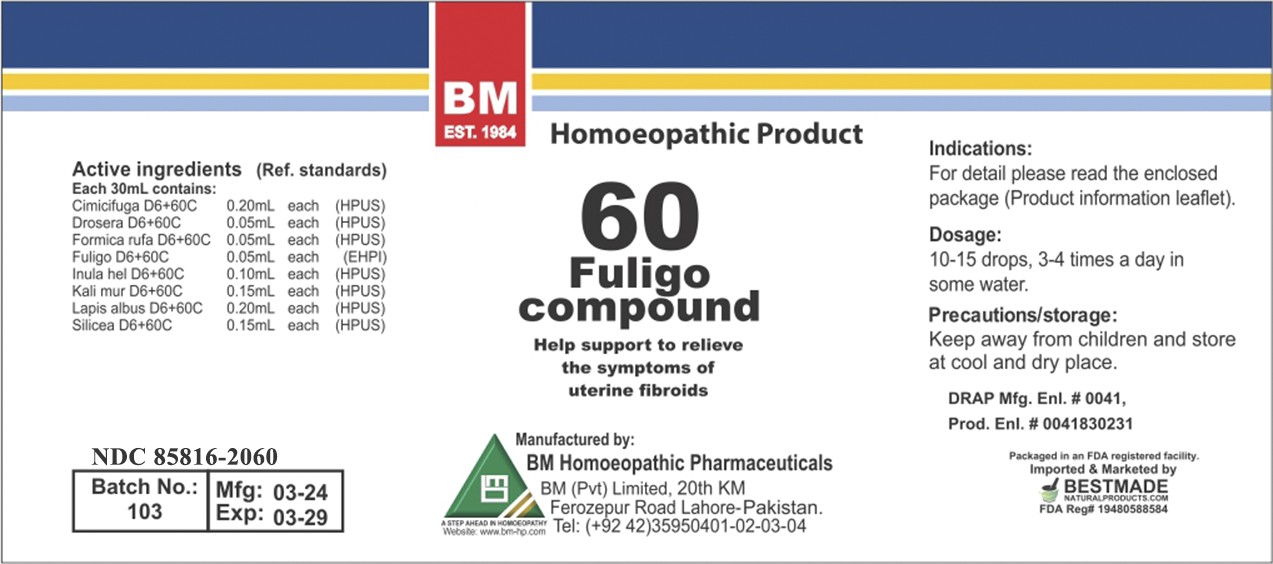 DRUG LABEL: Fuligo
NDC: 85816-2060 | Form: LIQUID
Manufacturer: BM Private Limited	
Category: homeopathic | Type: HUMAN OTC DRUG LABEL
Date: 20260212

ACTIVE INGREDIENTS: BLACK COHOSH 6 [hp_X]/1 mL; DROSERA ROTUNDIFOLIA WHOLE 6 [hp_X]/1 mL; SILICON DIOXIDE 6 [hp_X]/1 mL; CALCIUM HEXAFLUOROSILICATE 6 [hp_X]/1 mL; INULA HELENIUM ROOT 6 [hp_X]/1 mL; FORMICA RUFA 6 [hp_X]/1 mL; POTASSIUM CHLORIDE 6 [hp_X]/1 mL
INACTIVE INGREDIENTS: ALCOHOL 0.96 mL/1 mL

BM HOMEOPATHIC REMEDY LIQUIDS FULIGO/ BM60

DOSAGE AND ADMINISTRATION

10-15 drops, 3-4 times a day in some water

ACTIVE INGREDIENT

Cimicifuga, Drosera, Formica Rufa, Fuligo, Inula hel, kali mur, lapis albus, silicea

INACTIVE INGREDIENT

alcohol

INDICATIONS AND USAGE

For detail, please read the enclosed package (product information leaflet)

PURPOSE

For detail, please read the enclosed package (product information leaflet)

WARNINGS

Precautions/storage:
Keep away from children and store at cool and dry place.

KEEP OUT OF REACH OF CHILDREN

Precautions/storage:
Keep away from children and store at cool and dry place.

Package 1:

Package 2: